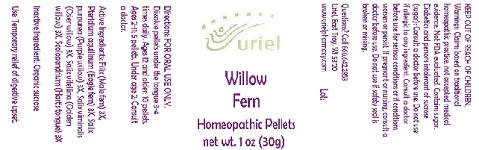 DRUG LABEL: Willow Fern
NDC: 48951-9160 | Form: PELLET
Manufacturer: Uriel Pharmacy Inc.
Category: homeopathic | Type: HUMAN OTC DRUG LABEL
Date: 20180607

ACTIVE INGREDIENTS: DRYOPTERIS FILIX-MAS ROOT 3 [hp_X]/1 1; PTERIDIUM AQUILINUM WHOLE 3 [hp_X]/1 1; SALIX PURPUREA BARK 3 [hp_X]/1 1; WILLOW BARK 3 [hp_X]/1 1; SALIX ALBA FLOWER 3 [hp_X]/1 1; ASPLENIUM SCOLOPENDRIUM TOP 3 [hp_X]/1 1
INACTIVE INGREDIENTS: SUCROSE

Willow Fern

INDICATIONS AND USAGE

Directions: FOR ORAL USE ONLY.

DOSAGE AND ADMINISTRATION

Dissolve pellets under the tongue 3-4 times daily. Ages 12 and older: 10 pellets. Ages 2-11: 5 pellets. Under age 2: Consult a doctor.

ACTIVE INGREDIENT

Active Ingredients: Filix (Male fern) 3X, Pteridium aquilinum (Eagle fern) 3X, Salix purpurea (Purple willow) 3X, Salix viminalis (Osier willow) 3X, Salix vitellina (Golden willow) 3X, Scolopendrium (Hart’s tongue) 3X

Inactive Ingredient: Organic sucrose

PURPOSE

Use: Temporary relief of digestive upset.

KEEP OUT OF REACH OF CHILDREN.

WARNINGS

Warnings: Claims based on traditional homeopathic practice, not accepted medical evidence. Not FDA evaluated. Contains sugar. Diabetics and persons intolerant of sucrose (sugar): Consult a doctor before use. Do not use if allergic to any ingredient. Consult a doctor before use for serious conditions or if conditions worsen or persist. If pregnant or nursing, consult a doctor before use. Do not use if safety seal is broken or missing.

QUESTIONS

Questions? Call 866.642.2858 Uriel, East Troy, WI 53120 www.urielpharmacy.com